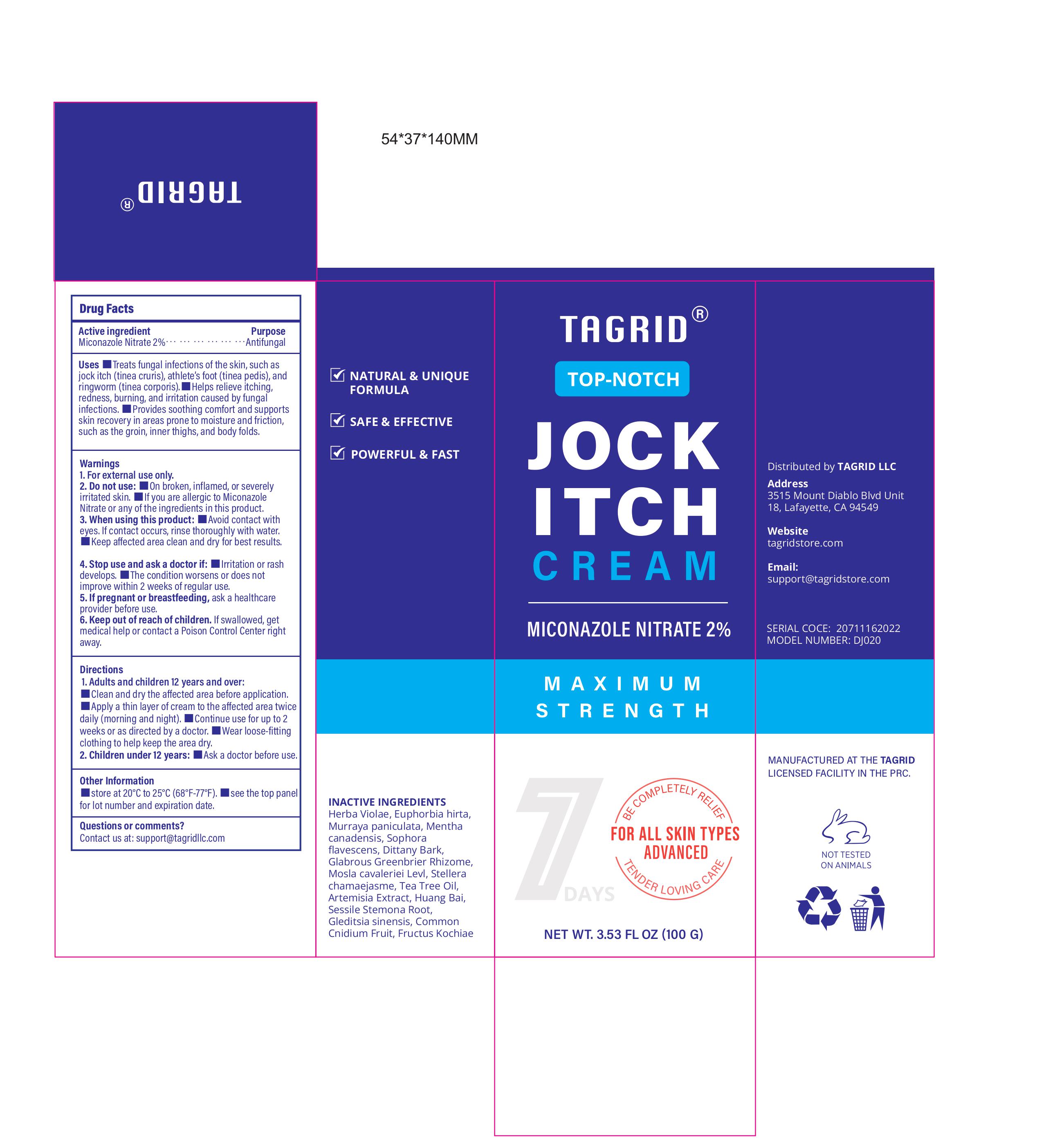 DRUG LABEL: Tagri Jock Itck Cream Miconazole Nitrate 2%
NDC: 85384-0003 | Form: CREAM
Manufacturer: TAGRID LLC
Category: otc | Type: HUMAN OTC DRUG LABEL
Date: 20250331

ACTIVE INGREDIENTS: MICONAZOLE NITRATE 20 mg/1 g
INACTIVE INGREDIENTS: EUPHORBIA HIRTA; ARTEMISIA CARUIFOLIA LEAF; STEMONA SESSILIFOLIA ROOT; VIOLA PHILIPPICA WHOLE; SOPHORA FLAVESCENS ROOT; TEA TREE OIL; MURRAYA PANICULATA ROOT BARK; PHELLODENDRON CHINENSE WHOLE; MENTHA CANADENSIS TOP; SMILAX GLABRA TUBER; MOSLA CAVALERIEI WHOLE; STELLERA CHAMAEJASME WHOLE; CNIDIUM MONNIERI FRUIT; BASSIA SCOPARIA FRUIT; DICTAMNUS ALBUS ROOT BARK; GLEDITSIA SINENSIS FRUIT

ACTIVE INGREDIENT

Miconazole Nitrate

PURPOSE

Antifungal

INDICATIONS AND USAGE

-Treats fungal infections of the skin, such as jock itch (tinea cruris), athlete's foot (tinea pedis), and
ringworm (tinea corporis).

-Helps relieve itching redness, burning, and irritation caused by fungal
infections.

-Provides soothing comfort and supports skin recovery in areas prone to moisture and friction,
such as the groin, inner thighs, and body folds.

WARNINGS

For external use only

Do not use: On broken, inflamed, or severely irritated skin.

lf you are allergic to Miconazole Nitrate or any of the ingredients in this product.

When using this product: Avoid contact with eyes.

If contact occurs, rinse thoroughly with water. Keep affected area clean and dry for best results.

Stop use and ask a doctor if: əlrritation or rash develops.

The condition worsens or does not improve within 2 weeks of regular use.

PREGNANCY OR BREAST FEEDING

If pregnant or breastfeeding, ask a healthcare provider before use.

Keep out of reach of children.

If swallowed, get medical help or contact a Poison Control Center right away.

DOSAGE AND ADMINISTRATION

1. Adults and children 12 years and over:
-Clean and dry the affected area before application.
-Apply a thin layer of cream to the affected area twice
daily (morning and night).
-Continue use for up to 2 weeks or as directed by a doctor.
Wear loose-fitting clothing to help keep the area dry.
2. Children under 12 years:
Ask a doctor before use.

OTHER SAFETY INFORMATION

store at 20°C to 25°C (68°F-77°F).
see the top panel for lot number and expiration date.

Questions or comments?
Contact us at: support@tagridllc.com

INACTIVE INGREDIENT

Herba Violae,

Euphorbia hirta,
Murraya paniculata,

Mentha canadensis,

Sophora flavescens,

Dittany Bark,
Glabrous Greenbrier Rhizome,
Mosla cavaleriei Levl,

Stellera chamaejasme,

Tea Tree Oil,
Artemisia Extract,

Huang Bai,
Sessile Stemona Root,
Gleditsia sinensis,

Common Cnidium Fruit,

Fructus Kochiae